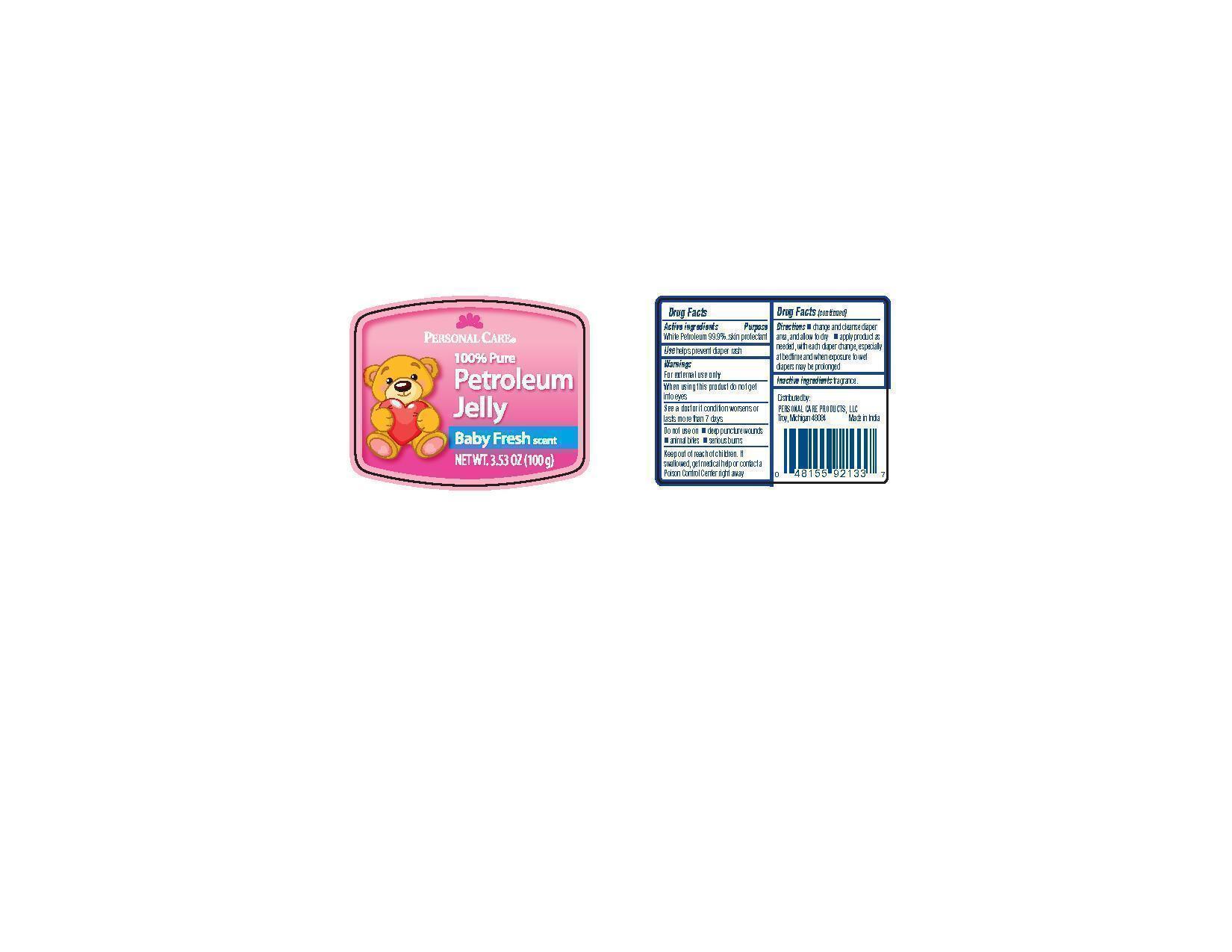 DRUG LABEL: Petroleum
                
                
                
NDC: 29500-8040 | Form: JELLY
Manufacturer: Personal Care Products
Category: otc | Type: HUMAN OTC DRUG LABEL
Date: 20120628

ACTIVE INGREDIENTS: Petrolatum 99.9 g/100 g
INACTIVE INGREDIENTS: water

Personal Care

Active ingredients

White Petroleum 99.9%

Purpose skin protectant

Keep out of reach of children. If swallowed, get medical help or contact a Poison Control Center right away.

Use

helps prevent diaper rash

Warnings

For external use only

When using this product do not get into eyes

See a doctor if condition worsens or lasts more than 7 days. Do not use on deep puncture wounds, animal bites, serious burns.

Directions

change and cleanse diaper area, and allow to dry

apply product as needed, with each diaper change, especially at bedtime and when exposure to wet diapers may be prolonged.

Inactive ingredients fragrance

PACKAGE LABEL

Personal Care

100% Pure Petroleum Jelly

Baby fresh scent

net wt. 3.52 oz (100 g)

Distributed by: Personal Care products, LLC

Troy, Michigan 48084 Made in India